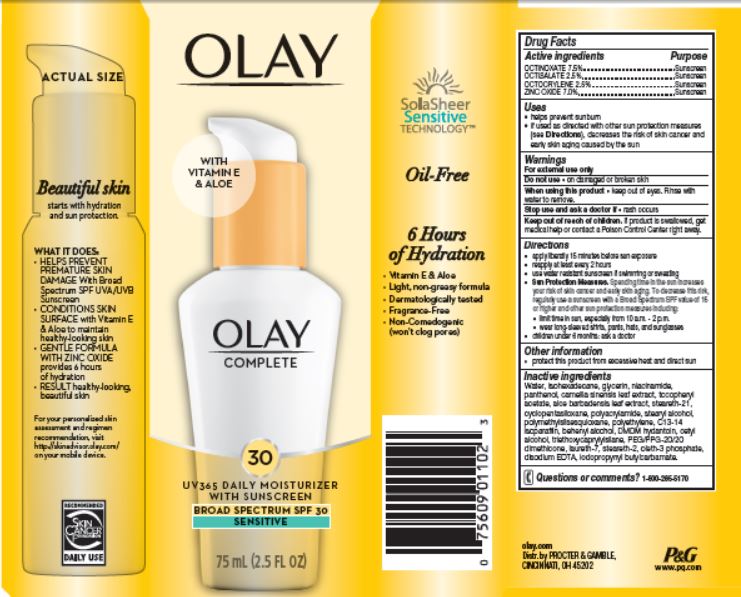 DRUG LABEL: Olay Complete UV365 Daily Moisturizer with Sunscreen
NDC: 69423-258 | Form: LOTION
Manufacturer: The Procter & Gamble Manufacturing Company
Category: otc | Type: HUMAN OTC DRUG LABEL
Date: 20251218

ACTIVE INGREDIENTS: OCTINOXATE 7.5 g/100 mL; OCTISALATE 2.5 g/100 mL; OCTOCRYLENE 2.5 g/100 mL; ZINC OXIDE 7 g/100 mL
INACTIVE INGREDIENTS: WATER; ISOHEXADECANE; GLYCERIN; STEARETH-21; GREEN TEA LEAF; ALOE VERA LEAF; PANTHENOL; NIACINAMIDE; CYCLOMETHICONE 5; STEARYL ALCOHOL; HIGH DENSITY POLYETHYLENE; DOCOSANOL; DMDM HYDANTOIN; .ALPHA.-TOCOPHEROL ACETATE; CETYL ALCOHOL; TRIETHOXYCAPRYLYLSILANE; PEG/PPG-20/20 DIMETHICONE; LAURETH-7; STEARETH-2; OLETH-3 PHOSPHATE; EDETATE DISODIUM; IODOPROPYNYL BUTYLCARBAMATE; C13-14 ISOPARAFFIN

Olay® Complete 30 UV365 Moisturizer with Sunscreen
Broad Spectrum SPF 30 Sensitive

Drug Facts

ACTIVE INGREDIENT

Active ingredients | Purpose
Octinoxate 7.5% | Sunscreen
Octisalate 2.5% | Sunscreen
Octocrylene 2.5% | Sunscreen
Zinc oxide 7.0% | Sunscreen

Uses

- helps prevent sunburn
- if used as directed with other sun protection measures (see Directions), decreases the risk of skin cancer and early skin aging caused by the sun

Warnings

For external use only

Do not use

- on damaged or broken skin

When using this product

- keep out of eyes. Rinse with water to remove.

Stop use and ask a doctor if

- rash occurs

Keep out of reach of children. If product is swallowed, get medical help or contact a Poison Control Center right away.

Directions

- apply liberally 15 minutes before sun exposure
- reapply at least every 2 hours
- use water resistant sunscreen if swimming or sweating
- Sun Protection Measures. Spending time in the sun increases your risk of skin cancer and early skin aging. To decrease this risk, regularly use a sunscreen with a Broad Spectrum SPF value of 15 or higher and other sun protection measures including:
  - limit time in sun, especially from 10 a.m. - 2 p.m.
  - wear long-sleeved shirts, pants, hats, and sunglasses
- children under 6 months: ask a doctor

Other information

- protect this product from excessive heat and direct sun

Inactive ingredients

Water, isohexadecane, glycerin, niacinamide, panthenol, camellia sinensis leaf extract, tocopheryl acetate, aloe barbadensis leaf extract, steareth-21, cyclopentasiloxane, polyacrylamide, stearyl alcohol, polymethylsilsesquioxane, polyethylene, C13-14 isoparaffin, behenyl alcohol, DMDM hydantoin, cetyl alcohol, triethoxycaprylylsilane, PEG/PPG-20/20 dimethicone, laureth-7, steareth-2, oleth-3 phosphate, disodium EDTA, iodopropynyl butylcarbamate.

Questions or comments?

Call 1-800-285-5170

Distr. by
PROCTER & GAMBLE,
CINCINNATI, OH 45202

PACKAGE LABEL

OLAY ®

COMPLETE

30

UV365 Daily Moisturizer
with sunscreen

BROAD SPECTRUM SPF 30
SENSITIVE

75 mL (2.5 FL OZ)